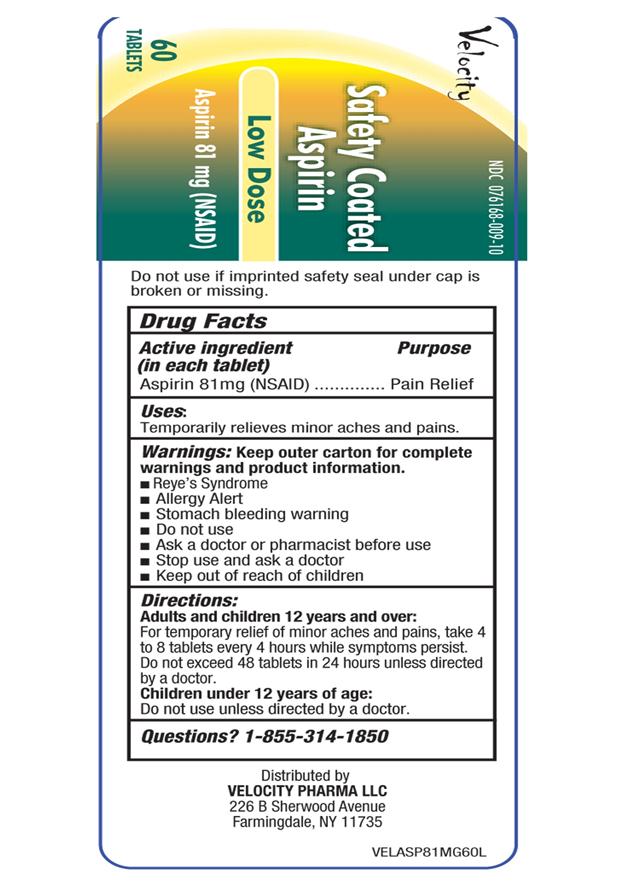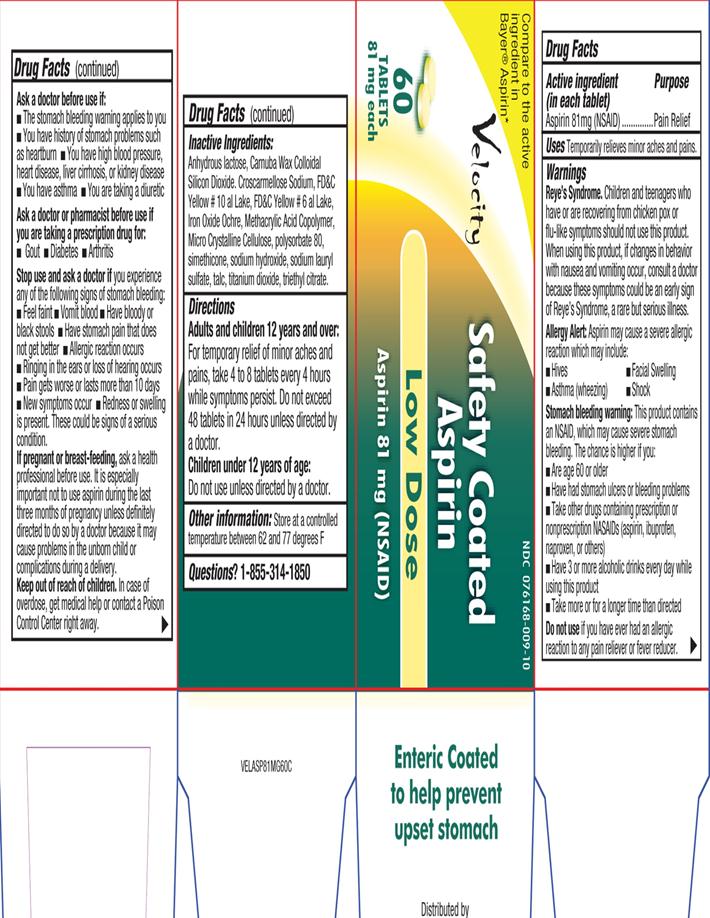 DRUG LABEL: Aspirin
NDC: 76168-009 | Form: TABLET
Manufacturer: Velocity Pharma
Category: otc | Type: HUMAN OTC DRUG LABEL
Date: 20131023

ACTIVE INGREDIENTS: ASPIRIN 81 mg/1 1
INACTIVE INGREDIENTS: CARNAUBA WAX; ANHYDROUS LACTOSE; CROSCARMELLOSE SODIUM; D&C YELLOW NO. 10; FD&C YELLOW NO. 6; BROWN IRON OXIDE; METHACRYLIC ACID; CELLULOSE, MICROCRYSTALLINE; POLYSORBATE 80; DIMETHICONE; SODIUM HYDROXIDE; SODIUM LAURYL SULFATE; TALC; TITANIUM DIOXIDE; TRIETHYL CITRATE

ASPIRIN 81mg

Active Ingredient

(in each tablet)

Aspirin 81 mg (NSAID)

Purpose

Pain Relief

Uses

- temporarily relieves minor aches and pains

Warnings

Reye’s Syndrome: Children and teenagers who have or are recovering from chicken pox or flu-like symptoms should not use this product. When using this product, if changes in behavior with nausea and vomiting occur, consult a doctor because these symptoms could be an early sign of Reye’s syndrome, a rare but serious illness.

Allergy Alert: Aspirin may cause a severe allergic reaction which may include:

- Hives
- Asthma (wheezing)
- Shock
- Facial Swelling
  Stomach Bleeding Warning: This product contains an NSAID, which may cause severe stomach bleeding. The chance is higher if you:
- Are age 60 or older
- have had stomach ulcers or bleeding problems
- take other drugs containing prescription or nonprescription NSAIDs (aspirin, ibuprofen, naproxen or others)
- have 3 or more alcoholic drinks every day while using this product
- takes more or for a longer time than directed
  Do not use
- if you have ever had an allergic reaction to any pain reliever or fever reducer.
  Ask a doctor before use if:
- The stomach bleeding warning applies to you
- You have history of stomach problems such as heartburn
- You have high blood pressure, heart disease, liver cirrhosis, or kidney disease
- You have asthma
- You are taking a diuretic
  Ask a doctor or pharmacist before use if you are taking a prescription drug for :
- Gout
- Diabetes
- Arthritis
  Stop use and ask a doctor if
- you experiences any of the following signs of stomach bleeding:
- feels faint
- vomits blood
- has bloody or black stools
- has stomach pain that does not get better
- pain gets worse or lasts more than 10 days
- New symptoms occur
- redness or swelling is present
- ringing in the ears or a loss of hearing occurs
  These could be signs of serious conditions.
  If pregnant or breast-feeding, ask a health professional before use. It is especially important not to use aspirin during the last 3 months of pregnancy unless definitely directed to do so by a doctor because it may cause problems in the unborn child or complications during delivery.

Keep out of reach of children.

In case of overdose, get medical help or contact a Poison Control Center right away.

Directions

Adults and Children 12 years and over:

For temporary relief of minor aches and pains, take 4 to 8 tablets every 4 hours while symptoms persist. Do not exceed 48 tablets in 24 hours unless directed by a doctor.

Children under 12 years of age: Do not use unless directed by a doctor.

Other Information

- Store at a controlled temperature between 62 and 77 degrees F

Inactive Ingredients

Anhydrous Lactose, Carnuba Wax Colloidal Sillicon Dioxide, Crosscarmellose Sodium,FD&C Yellow #10 al lake, FD&C Yellow#6 al Lake, Iron Oxide Ochre, Methacrylic acid copolymer, Micro crystalline cellulose, Polysorbate 80, simethiocone, sodium hydroxide, sodium lauryl sulfate, talc, titanium dioxide, triethyl citrate.

Questions?

Call 1-855-314-1850

TAMPER EVIDENT: DO NOT USE IF IMPRINTED SAFETY SEAL UNDER CAP IS BROKEN OR MISSING

Distributed by: Velocity Pharma LLC

PACKAGE LABEL.PRINCIPAL DISPLAY PANEL

NDC: 76168-009-10 –60 COUNT

Enteric Coated to help prevent upset stomach